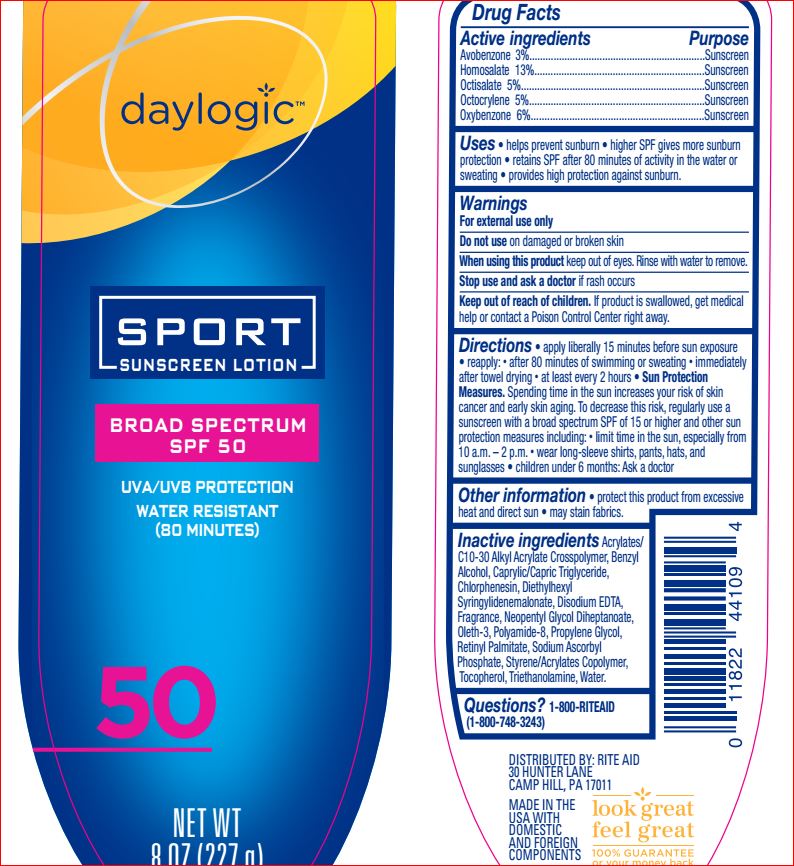 DRUG LABEL: Sport Sunscreen SPF 50
NDC: 11822-7794 | Form: LOTION
Manufacturer: Rite Aid
Category: otc | Type: HUMAN OTC DRUG LABEL
Date: 20180813

ACTIVE INGREDIENTS: Avobenzone 3 g/100 mL; Homosalate 13 g/100 mL; Octisalate 5 g/100 mL; Octocrylene 5 g/100 mL; Oxybenzone 6 g/100 mL
INACTIVE INGREDIENTS: CARBOMER INTERPOLYMER TYPE A (ALLYL SUCROSE CROSSLINKED); Benzyl Alcohol; MEDIUM-CHAIN TRIGLYCERIDES; Chlorphenesin; Diethylhexyl Syringylidenemalonate; EDETATE DISODIUM; Neopentyl Glycol Diheptanoate; Oleth-3; Propylene Glycol; VITAMIN A PALMITATE; Sodium Ascorbyl Phosphate; .ALPHA.-TOCOPHEROL ACETATE; TROLAMINE; WATER

Drug Facts

Active ingredients Purpose
Avobenzone 3%...........................................Sunscreen
Homosalate 13%.........................................Sunscreen
Octisalate 5%..............................................Sunscreen
Octocrylene 5%...........................................Sunscreen
Oxybenzone 6%..........................................Sunscreen

INDICATIONS AND USAGE

Uses • helps prevent sunburn

Warnings
For external use only
Do not use on damaged or broken skin
When using this product keep out of eyes. Rinse
with water to remove.
Stop use and ask a doctor if rash occurs

Keep out of reach of children. If product is swallowed, get medical help or contact a Poison Control Center right away.

Directions

• apply liberally 15 minutes
before sun exposure • reapply: • after 80 minutes of
swimming or sweating • immediately after towel
drying • at least every 2 hours • Sun Protection
Measures. Spending time in the sun increases your
risk of skin cancer and early skin aging. To
decrease this risk, regularly use a sunscreen with a
broad spectrum SPF of 15 or higher and other sun
protection measures including: • limit time in the
sun, especially from 10 a.m. – 2 p.m. • wear
long-sleeve shirts, pants, hats, and sunglasses
• children under 6 months: Ask a doctor

Other information
• protect this product from excessive heat and
direct sun • may stain fabrics

Inactive ingredients

Water,
Propylene Glycol, Neopentyl Glycol Diheptanoate,
Polyamide-8, Styrene/Acrylates Copolymer,
Tocopherol, Retinyl Palmitate, Acrylates/C10-30
Alkyl Acrylate Crosspolymer, Benzyl Alcohol,
Caprylic/Capric Triglyceride, Chlorphenesin,
Diethylhexyl Syringylidenemalonate, Disodium
EDTA, Oleth-3, Sodium Ascorbyl Phosphate,
Triethanolamine, Fragrance.